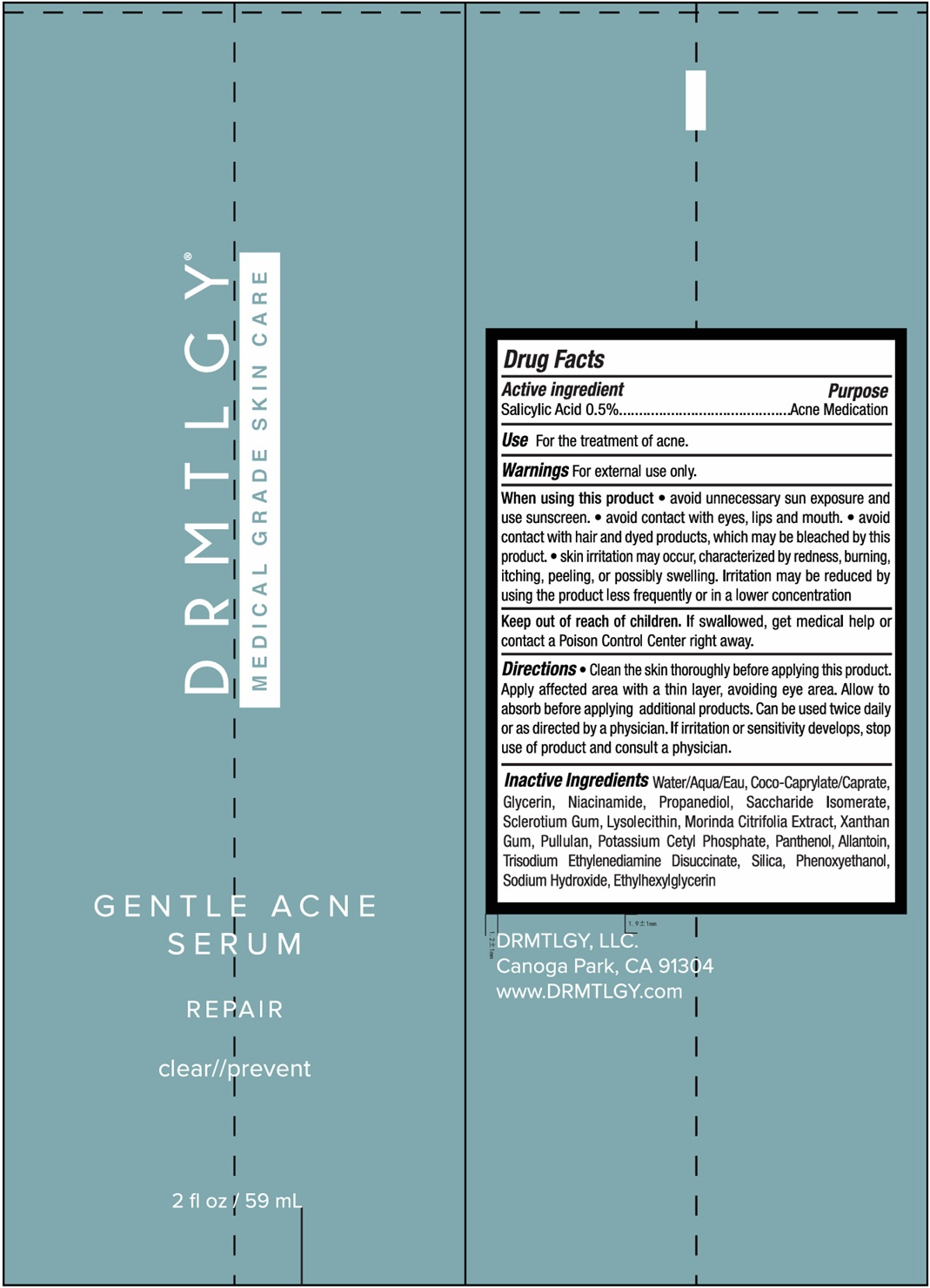 DRUG LABEL: GENTLE ACNE SERUM
NDC: 83286-016 | Form: GEL
Manufacturer: Drmtlgy, LLC
Category: otc | Type: HUMAN OTC DRUG LABEL
Date: 20251010

ACTIVE INGREDIENTS: SALICYLIC ACID 0.5 g/100 mL
INACTIVE INGREDIENTS: WATER; COCOYL CAPRYLOCAPRATE; GLYCERIN; NIACINAMIDE; PROPANEDIOL; SACCHARIDE ISOMERATE; BETASIZOFIRAN; LYSOPHOSPHATIDYLCHOLINE, SOYBEAN; NONI FRUIT; XANTHAN GUM; PULLULAN; POTASSIUM CETYL PHOSPHATE; PANTHENOL; ALLANTOIN; TRISODIUM ETHYLENEDIAMINE DISUCCINATE; SILICON DIOXIDE; PHENOXYETHANOL; SODIUM HYDROXIDE; ETHYLHEXYLGLYCERIN

DRMTLGY® GENTLE ACNE SERUM

Active ingredient

Salicylic Acid 0.5%

Purpose

Acne Medication

Uses

For the treatment of acne.

Warnings

For external use only.

When using this product • avoid unnecessary sun exposure and use sunscreen. • avoid contact with eyes, lips and mouth. • avoid contact with hair and dyed products, which may be bleached by this product. • skin irritation may occur, characterized by redness, burning, itching, peeling, or possibly swelling. Irritation may be reduced by using the product less frequently or in a lower concentration

Keep out of reach of children. If swallowed, get medical help or contact a Poison Control Center right away.

Directions

• Clean the skin thoroughly before applying this product. Apply affected area with a thin layer, avoiding eye area. Allow to absorb before applying additional products. Can be used twice daily or as directed by a physician. If irritation or sensitivity develops, stop use of product and consult a physician.

Inactive Ingredients

Water/Aqua/Eau, Coco-Caprylate/Caprate, Glycerin, Niacinamide, Propanediol, Saccharide Isomerate, Sclerotium Gum, Lysolecithin, Morinda Citrifolia Extract, Xanthan Gum, Pullulan, Potassium Cetyl Phosphate, Panthenol, Allantoin, Trisodium Ethylenediamine Disuccinate, Silica, Phenoxyethanol, Sodium Hydroxide, Ethylhexylglycerin

MEDICAL GRADE SKIN CARE

REPAIR

clear//prevent

DRMTLGY, LLC
Canoga Park, CA 91304
www.DRMTLGY.com